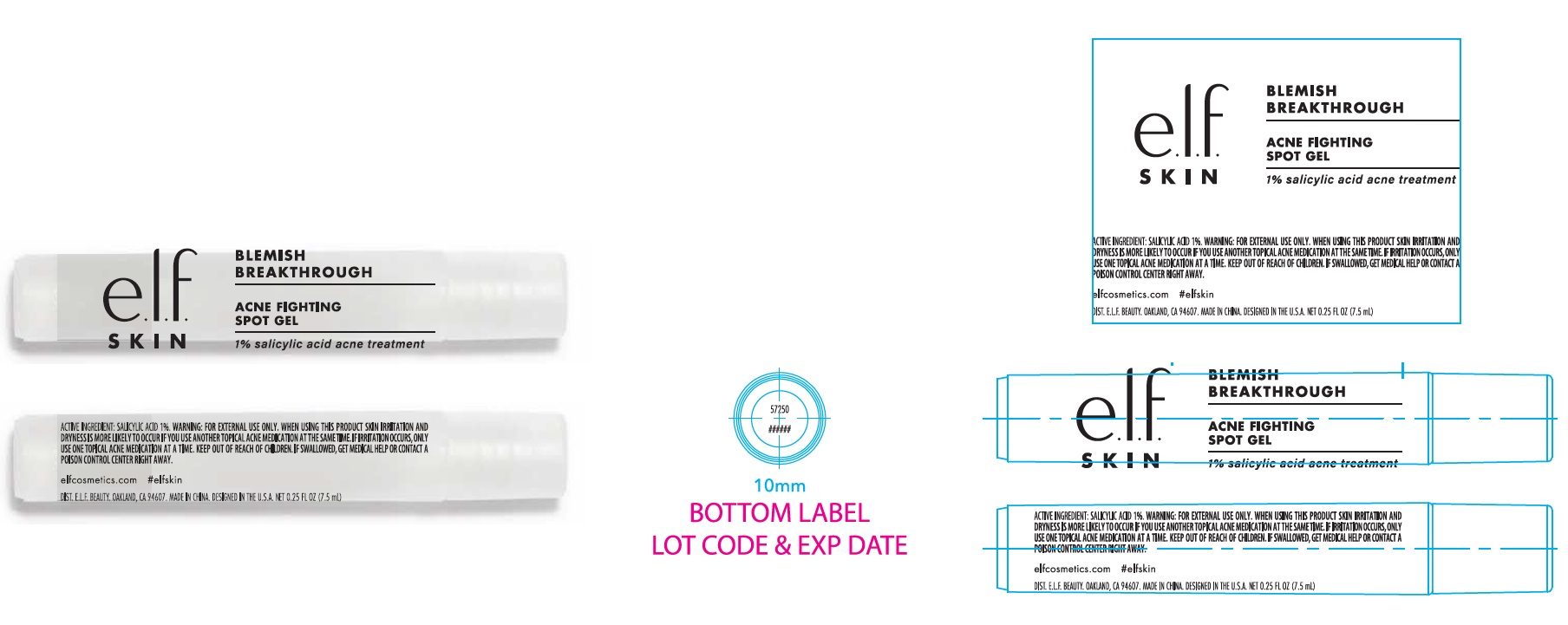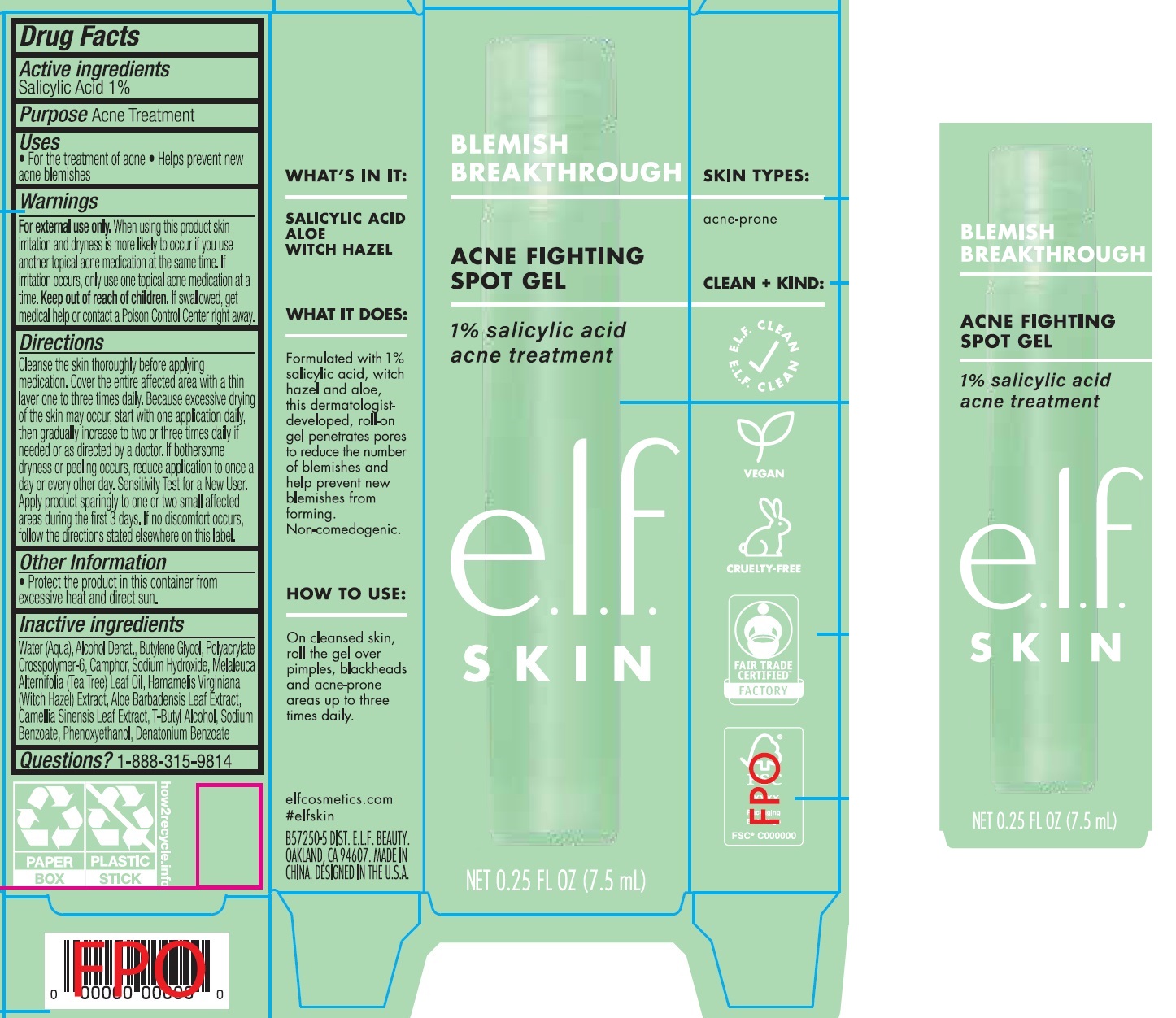 DRUG LABEL: Acne Fighting Spot Gel
NDC: 76354-414 | Form: GEL
Manufacturer: e.l.f. Cosmetics, Inc
Category: otc | Type: HUMAN OTC DRUG LABEL
Date: 20251021

ACTIVE INGREDIENTS: SALICYLIC ACID 10 mg/1 mL
INACTIVE INGREDIENTS: SODIUM BENZOATE; PHENOXYETHANOL; DENATONIUM BENZOATE; WATER; ALCOHOL; BUTYLENE GLYCOL; AMMONIUM ACRYLOYLDIMETHYLTAURATE, DIMETHYLACRYLAMIDE, LAURYL METHACRYLATE AND LAURETH-4 METHACRYLATE COPOLYMER, TRIMETHYLOLPROPANE TRIACRYLATE CROSSLINKED (45000 MPA.S); SODIUM HYDROXIDE; TEA TREE OIL; HAMAMELIS VIRGINIANA TOP; ALOE VERA LEAF; GREEN TEA LEAF; TERT-BUTYL ALCOHOL

Acne Fighting Spot Gel

Active ingredients

Salicylic Acid 1%

Purpose

Acne Treatment

Uses

- For the treatment of acne
- Helps prevent new acne blemishes

Warnings

For external use only.

When using this product

skin irritation and dryness is more likely to occur if you use another topical acne medication at the same time. If irritation occurs, only use one topical acne medication at a time.

Keep out of reach of children.

If swallowed, get medical help or contact a Poison Control Center right away.

Directions

Cleanse the skin thoroughly before applying medication. Cover the entire affected area with a thin layer one to three times daily. Because excessive drying of the skin may occur, start with one application daily, then gradually increase to two or three times daily if needed or as directed by a doctor. If bothersome dryness or peeling occurs, reduce application to once a day or every other day. Sensitivity Test for a New User. Apply product sparingly to one or two small affected areas during the first 3 days. If no discomfort occurs, follow the directions stated eleswhere on this label.

Other Information

- Protect the product in this container from excessive heat and direct sun.

Inactive ingredients

Water (Aqua), Alcohol Denat., Butylene Glycol, Polyacrylate Crosspolymer-6, Camphor, Sodium Hydroxide, Melaleuca Alternifolia (Tea Tree) Leaf Oil, Hamamelis Virginiana (Witch Hazel) Extract, Aloe Barbadensis Leaf Extract, Camellia Sinensis Leaf Extract, T-Butyl Alcohol, Sodium Benzoate, Phenoxyethanol, Denatonium Benzoate

Questions or comments

1-888-315-9814